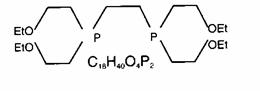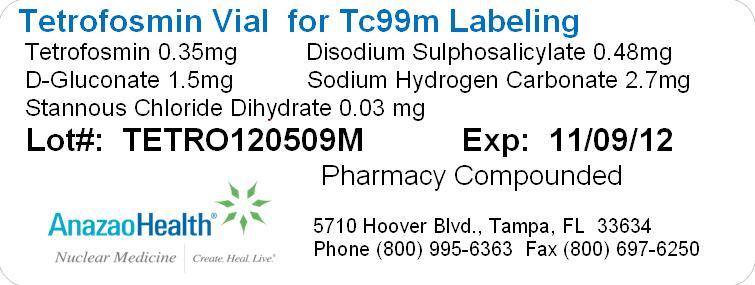 DRUG LABEL: Tetrofosmin
NDC: 51808-223 | Form: INJECTION, POWDER, LYOPHILIZED, FOR SOLUTION
Manufacturer: AnazaoHealth Corporation
Category: prescription | Type: HUMAN PRESCRIPTION DRUG LABEL
Date: 20120523

ACTIVE INGREDIENTS: TETROFOSMIN 0.35 mg/1 1
INACTIVE INGREDIENTS: DISODIUM SULFOSALICYLATE 0.48 mg/1 1; SODIUM BICARBONATE 2.7 mg/1 1; GLUCONIC ACID 1.5 mg/1 1

Tetrofosmin
(for the preparation of Tc99m Tetrofosmin injection)

Dear Medical Professional,

Per your order, we have compounded Tetrofosmin as a sterile, freeze-dried preparation in a 10 mL vial. The characteristics of this preparation are described below.

DESCRIPTION

AnazaoHealth’s compounded Tetrofosmin vial is a sterile, non-pyrogenic preparation that consists of a lyophilized mixture of 0.35 mg of Tetrofosmin, 1.5 mg of D-Gluconate, 0.03 mg of Stannous Chloride Dihydrate, 0.48 mg of Disodium Sulphosalicylate, and 2.7 mg of Sodium Hydrogen Carbonate and is maintained under an inert nitrogen atmosphere. It contains no antimicrobrial preservative.

INDICATIONS

Tetrofosmin is a diagnostic agent used to assess areas of reversible myocardial ischemia in the presence or absence of infracted myocardium and is also used to assess ventricular function.

PHYSICAL HALF-LIFE & TARGET ORGANS

The physical half-life of technetium, Tc99m, is 6 hours and has a principal radiation emission of gamma photons with a mean energy of 140 KeV.

Estimated Absorbed Radiation Dose (Technetium Tc99m Tetrofosmin Injection)
 | Absorbed radiation dose
 | Exercise |  | Rest
Target organ | rad/mCi | µGy/MBq | rad/mCi | µGy/MBq
Gall bladder wall | 0.123 | 33.2 | 0.180 | 48.6
Upper large intestine | 0.075 | 20.1 | 0.113 | 30.4
Bladder wall | 0.058 | 15.6 | 0.071 | 19.3
Lower large intestine | 0.057 | 15.3 | 0.082 | 22.2
Small intestine | 0.045 | 12.1 | 0.063 | 17.0
Kidney | 0.039 | 10.4 | 0.046 | 12.5
Salivary glands | 0.030 | 8.04 | 0.043 | 11.6
Ovaries | 0.029 | 7.88 | 0.035 | 9.55
Uterus | 0.027 | 7.34 | 0.031 | 8.36
Bone surface | 0.023 | 6.23 | 0.021 | 5.58
Pancreas | 0.019 | 5.00 | 0.018 | 4.98
Stomach | 0.017 | 4.60 | 0.017 | 4.63
Thyroid | 0.016 | 4.34 | 0.022 | 5.83
Adrenals | 0.016 | 4.32 | 0.015 | 4.11
Heart wall | 0.015 | 4.14 | 0.015 | 3.93
Red marrow | 0.015 | 4.14 | 0.015 | 3.97
Spleen | 0.015 | 4.12 | 0.014 | 3.82
Muscle | 0.013 | 3.52 | 0.012 | 3.32
Testes | 0.013 | 3.41 | 0.011 | 3.05
Liver | 0.012 | 3.22 | 0.015 | 4.15
Thymus | 0.012 | 3.11 | 0.009 | 2.54
Brain | 0.010 | 2.72 | 0.008 | 2.15
Lungs | 0.008 | 2.27 | 0.008 | 2.08
Skin | 0.008 | 2.22 | 0.007 | 1.91
Breasts | 0.008 | 2.22 | 0.007 | 1.83

Dose calculations were performed using the standard MIRD method (MIRD Pamphlet No.1 (rev),Society of Nuclear Medicine, 1976).

Effective dose equivalents (EDE) were calculated in accordance with ICRP 53 (Ann. ICRP 18 (1-4),1988) and gave values of 8.61 × 10-3 mSV/MBq and 1.12 × 10-2 mSV/MBq after exercise and rest, respectively.

CLINICAL PHARMACOLOGY

The structural formula for tetrofosmin is:

When Tetrofosmin is reconstituted with Tc99m pertechnetate, a complex of Tc99m Tetrofosmin is formed and is the active ingredient of the reconstituted product. When administered intravenously, Tc99m Tetrofosmin shows rapid myocardial uptake and its distribution follows a linear relationship with coronary blood flow.

Tc99m Tetrofosmin is a lipophilic agent that is taken up by the mitochondria of myocardial cells by passive diffusion and appears to accumulate in viable myocardial tissue.

CONTRAINDICATIONS

There are no known contraindications for this preparation.

DOSE AND ROUTE OF ADMINISTRATION

Depending on the protocol for rest/stress imaging, doses of 10 to 30 mCi (370 to 1110 MBq) are given intravenously

PREPARATION

1. Snap off the plastic lid and place in appropriate lead shielding. Wipe the septum with 70% isopropyl alcohol and allow it to dry.
2. Using a 10 mL syringe, dilute up to 360 mCi of Tc99m with saline and add to vial. The total volume should be between 6 mL -12 mL and the Tc99m concentration should not exceed 30 mCi/mL (360 mCi/12 mL).
3. After adding the Tc99m, insert a 0.22 µm filtered vent needle and, using a separate syringe, withdraw 3 mL of gas from the vial, allowing sterile filtered air into the vial. Remove vent needle and syringe.
4. Mix gently and invert several times for 10 seconds.
5. Let stand for 15 minutes at room temperature as the complexes form.
6. Inspect vial through a lead glass shield for particulate matter. Do not use if the solution is not clear.
7. Store at 2°- 8°C (36°- 46°F) and use within 12 hours after mixing. Radiochemical purity should be at least 90% prior to administration
8. QC info: Solvent – Ethyl Acetate, Strip – Whatman CHR% Tag = top counts/total counts X 100%

STORAGE

The preparation should be stored in the refrigerator at 2- 8(C (36 - 46(F) and protected from light.